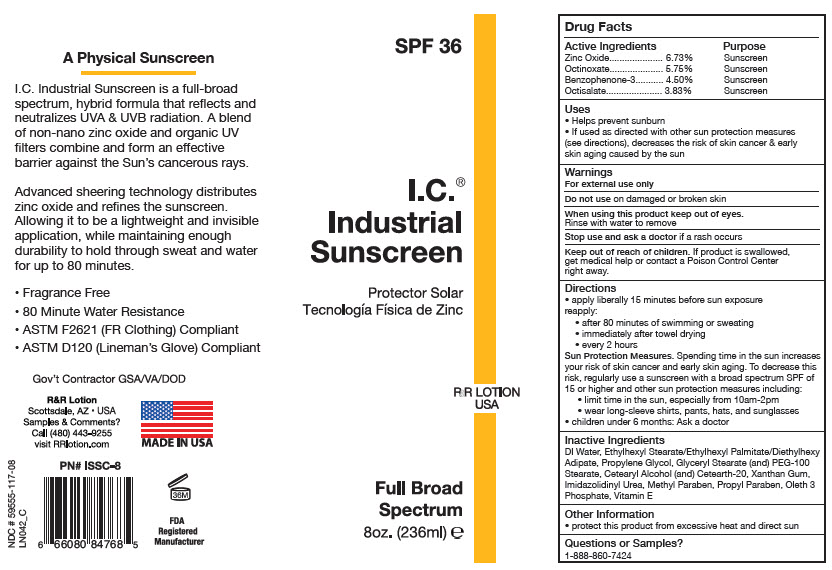 DRUG LABEL: I.C. Industrial Sunscreen
NDC: 59555-117 | Form: LOTION
Manufacturer: R & R Lotion, Inc
Category: otc | Type: HUMAN OTC DRUG LABEL
Date: 20250915

ACTIVE INGREDIENTS: ZINC OXIDE 67.3 mg/1 mL; OCTINOXATE 57.5 mg/1 mL; OXYBENZONE 45 mg/1 mL; OCTISALATE 38.3 mg/1 mL
INACTIVE INGREDIENTS: WATER; ETHYLHEXYL STEARATE; ETHYLHEXYL PALMITATE; DIETHYLHEXYL ADIPATE; PROPYLENE GLYCOL; GLYCERYL MONOSTEARATE; PEG-100 MONOSTEARATE; CETOSTEARYL ALCOHOL; POLYOXYL 20 CETOSTEARYL ETHER; XANTHAN GUM; IMIDUREA; METHYLPARABEN; PROPYLPARABEN; OLETH-3 PHOSPHATE; .ALPHA.-TOCOPHEROL ACETATE

I.C.® Industrial Sunscreen

Drug Facts

ACTIVE INGREDIENT

Active Ingredients |  | Purpose
Zinc Oxide | 6.73% | Sunscreen
Octinoxate | 5.75% | Sunscreen
Benzophenone-3 | 4.50% | Sunscreen
Octisalate | 3.83% | Sunscreen

Uses

- Helps prevent sunburn
- If used as directed with other sun protection measures (see directions), decreases the risk of skin cancer & early skin aging caused by the sun

Warnings

For external use only

Do not use on damaged or broken skin

When using this product keep out of eyes.

Rinse with water to remove

Stop use and ask a doctor if a rash occurs

Keep out of reach of children. If product is swallowed, get medical help or contact a Poison Control Center right away.

Directions

- apply liberally 15 minutes before sun exposure reapply:
  - after 80 minutes of swimming or sweating
  - immediately after towel drying
  - every 2 hours
  Sun Protection Measures. Spending time in the sun increases your risk of skin cancer and early skin aging. To decrease this risk, regularly use a sunscreen with a broad spectrum SPF of 15 or higher and other sun protection measures including:
  - limit time in the sun, especially from 10am-2pm
  - wear long-sleeve shirts, pants, hats, and sunglasses
- children under 6 months: Ask a doctor

Inactive Ingredients

DI Water, Ethylhexyl Stearate/Ethylhexyl Palmitate/Diethylhexy Adipate, Propylene Glycol, Glyceryl Stearate (and) PEG-100 Stearate, Cetearyl Alcohol (and) Cetearth-20 Xanthan Gum, Imidazolidinyl Urea, Methyl Paraben, Propyl Paraben, Oleth 3 Phosphate, Vitamin E

Other Information

- protect this product from excessive heat and direct sun

Questions or Samples?

1-888-860-7424

PRINCIPAL DISPLAY PANEL - 236 ml Bottle Label

SPF 36

I.C.®
Industrial
Sunscreen

R&R LOTION
USA

Full Broad
Spectrum
8oz. (236ml) ℮